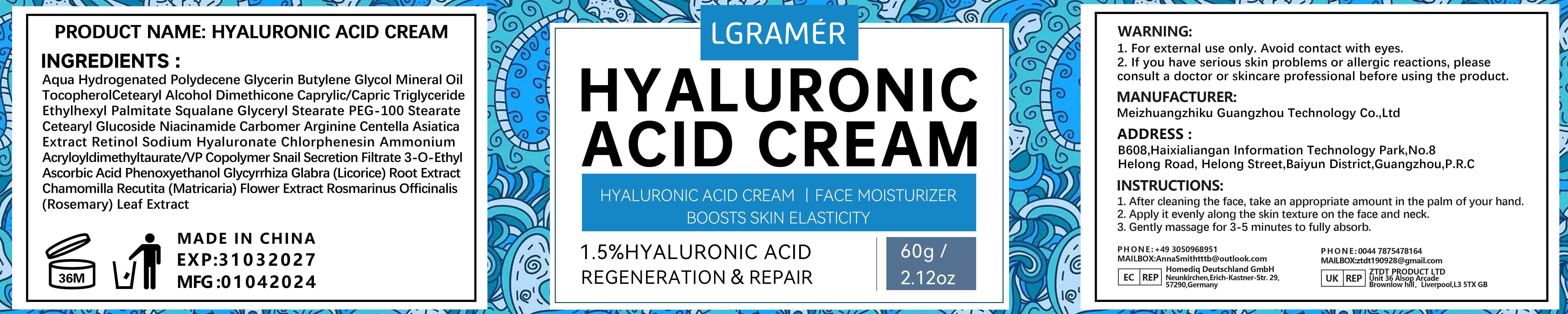 DRUG LABEL: LGRAMERHyaluronicacidfacialcarecream
NDC: 84350-006 | Form: CREAM
Manufacturer: Shenzhen Sihal Juntong Technology Co. Ltd
Category: otc | Type: HUMAN OTC DRUG LABEL
Date: 20240830

ACTIVE INGREDIENTS: SQUALANE 1 g/60 mg
INACTIVE INGREDIENTS: WATER

ACTIVE INGREDIENT

1.5%YALURONIC ACID

INACTIVE INGREDIENT

Waler 5%水的5%

PURPOSE

Moisturizing 保湿

Do not use 不要使用

lf you have allergic reactions, stop to use如有过敏反应，请停止使用

when using this product

1.After cleansing the body, take an appropriate amount of foot cream on the palm of your hand

2. Gently apply it evenly on the desired area
3. Massage gently until fuly absorbed.

Keep out of reach of children

use

INSTRUCTIONS:
1.After cleansing the body, take an appropriate amount of foot cream on the palm of your hand

2. Gently apply it evenly on the desired area
3. Massage gently until fully absorbed.

Dosage and administration 剂量和给药方法

appropiate amount 适量

PACKAGE LABEL

60g NDC 84350-006-06